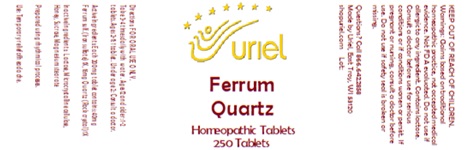 DRUG LABEL: Ferrum Quartz
NDC: 48951-4197 | Form: TABLET
Manufacturer: Uriel Pharmacy, Inc.
Category: homeopathic | Type: HUMAN OTC DRUG LABEL
Date: 20250801

ACTIVE INGREDIENTS: FERROUS SULFATE 1 [hp_X]/1 1; SULFUR 1 [hp_X]/1 1
INACTIVE INGREDIENTS: MICROCRYSTALLINE CELLULOSE; MAGNESIUM STEARATE; SUCROSE; LACTOSE, UNSPECIFIED FORM; HONEY

Ferrum Quartz

INDICATIONS AND USAGE

Directions: FOR ORAL USE ONLY.

DOSAGE AND ADMINISTRATION

Take 3-4 times daily with water. Ages 12 and older: 1-2 tablets. Ages 2-11: 1 tablet. Under age 2: Consult a doctor.

ACTIVE INGREDIENT

Active Ingredients: Each 200mg tablet contains: 40mg Ferrum sulf. (Iron sulfate) 1X, 16mg Quartz (Rock crystal) 1X

INACTIVE INGREDIENT

Inactive Ingredients: Microcrystalline cellulose, Honey, Sucrose, Magnesium stearate, Lactose

Prepared using rhythmical processes.

PURPOSE

Use: Temporary relief of headache.

KEEP OUT OF REACH OF CHILDREN.

WARNINGS

Warnings: Claims based on traditional homeopathic practice, not accepted medical evidence. Not FDA evaluated. Do not use if allergic to any ingredient. Contains lactose. Consult a doctor before use for serious conditions or if conditions worsen or persist. If pregnant or nursing, consult a doctor before use. Do not use if safety seal is broken or missing.

Questions? Call 866.642.2858
Made by Uriel, East Troy, WI 53120
shopuriel.com Lot: